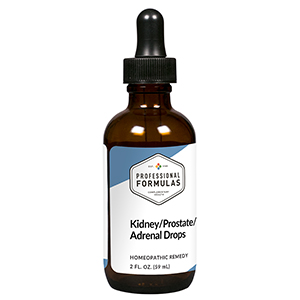 DRUG LABEL: Kidney/Prostate/Adrenal Drops
NDC: 63083-5011 | Form: LIQUID
Manufacturer: Professional Complementary Health Formulas
Category: homeopathic | Type: HUMAN OTC DRUG LABEL
Date: 20190815

ACTIVE INGREDIENTS: PRASTERONE 6 [hp_X]/59 mL; PREGNENOLONE 6 [hp_X]/59 mL; SUS SCROFA ADRENAL GLAND 6 [hp_X]/59 mL; BEEF KIDNEY 6 [hp_X]/59 mL; BOS TAURUS PROSTATE GLAND 6 [hp_X]/59 mL
INACTIVE INGREDIENTS: ALCOHOL; WATER

HKPA

ACTIVE INGREDIENTS

Dehydroepiandrosterone (DHEA) 6X
Pregnenolone 6X
Adrenal 6X, 12X, 30X, 60X, 100X
Kidney 6X, 12X, 30X, 60X, 100X
Prostate 6X, 12X, 30X, 60X, 100X

QUESTIONS

Professional Formulas

PO Box 2034 Lake Oswego, OR 97035

INDICATIONS

For the temporary relief of frequent or difficult urination, a feeling of urgency to urinate, decreased sexual desire or satisfaction, anxiousness, muscle cramps, lethargy, or fatigue.*

PURPOSE

*Claims based on traditional homeopathic practice, not accepted medical evidence. Not FDA evaluated.

WARNINGS

Consult a doctor if condition worsens or if symptoms persist. Keep out of the reach of children. In case of overdose, get medical help or contact a poison control center right away. If pregnant or breastfeeding, ask a healthcare professional before use.

Keep out of the reach of children.

PREGNANCY OR BREAST FEEDING

If pregnant or breastfeeding, ask a healthcare professional before use.

DIRECTIONS

Place drops under tongue 30 minutes before/after meals. Adults and children 12 years and over: Take 10 drops up to 3 times per day. Consult a physician for use in children under 12 years of age.

OTHER INFORMATION

Tamper resistant. If seal is broken, do not use. After opening, close container tightly and store at room temperature away from heat.

INACTIVE INGREDIENTS

20% ethanol, purified water.

LABEL

Est 1985

Professional Formulas

Complementary Health

Kidney/Prostate/Adrenal Drops

Homeopathic Remedy

2 FL. OZ. (59 mL)